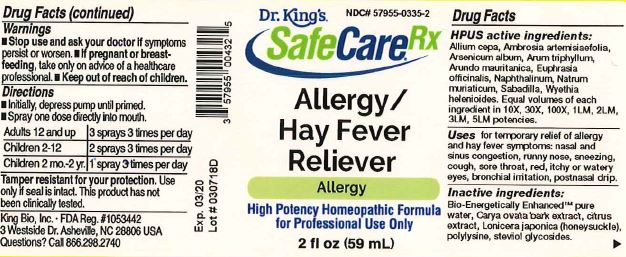 DRUG LABEL: Allergy Hay Fever Reliever
NDC: 57955-0335 | Form: LIQUID
Manufacturer: King Bio Inc.
Category: homeopathic | Type: HUMAN OTC DRUG LABEL
Date: 20180531

ACTIVE INGREDIENTS: ONION 10 [hp_X]/59 mL; AMBROSIA ARTEMISIIFOLIA 10 [hp_X]/59 mL; ARSENIC TRIOXIDE 10 [hp_X]/59 mL; ARISAEMA TRIPHYLLUM ROOT 10 [hp_X]/59 mL; ARUNDO PLINIANA ROOT 10 [hp_X]/59 mL; EUPHRASIA STRICTA 10 [hp_X]/59 mL; NAPHTHALENE 10 [hp_X]/59 mL; SODIUM CHLORIDE 10 [hp_X]/59 mL; SCHOENOCAULON OFFICINALE SEED 10 [hp_X]/59 mL; WYETHIA HELENIOIDES ROOT 10 [hp_X]/59 mL
INACTIVE INGREDIENTS: WATER; CARYA OVATA BARK; CITRUS BIOFLAVONOIDS; LONICERA JAPONICA FLOWER; POLYEPSILON-LYSINE (4000 MW); REBAUDIOSIDE A

Allergy Hay Fever Reliever™

ACTIVE INGREDIENT

Drug Facts__________________________________________________________________________________________________________

HPUS active ingredients: Allium cepa, Ambrosia artemisiaefolia, Arsenicum album, afrum triphyllum, Arundo mauritanica, Euphrasia officinalis, Naphthalinum, Natrum muriaticum, Sabadilla, Wyethia helenioides. Equal volumes of each ingredient in 10X, 30X, 100X, 1LM, 2LM, 3LM, 5LM potencies.

INDICATIONS AND USAGE

Uses temporary relief of allergy and hay fever symptoms: nasal and sinus congestion, runny nose, sneezing, cough, sore throat, red, itchy or watery eyes, bronchial irritation, postnasal drip.

Inactive Ingredients:

Bio-Energetically Enhanced™ pure water, Carya ovata bark extract, citrus extract, Lonicera japonica (honeysuckle), polylysine, steviol glycosides.

Warnings

- Stop use and ask your doctor if symptoms persist or worsen.
- If pregnant or breast-feeding, take only on advice of a healthcare professional.

- Keep out of reach of children.

Directions

- Initially, depress pump until primed.
- Spray one dose directly into mouth.
- Adults 12 and up: 3 sprays 3 times per day.
- Children 2-12: 2 sprays 3 times per day.
- Children 2mo-2yr: 1 spray 3 times per day.

OTHER SAFETY INFORMATION

Tamper resistant for your protection. Use only if safety seal is intact. This product has not been clinically tested.

PURPOSE

Uses temporary relief of allergy and hay fever symptoms: nasal and sinus congestion, runny nose, sneezing, cough, sore throat, red, itchy or watery eyes, bronchial irritation, postnasal drip.